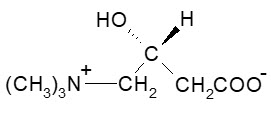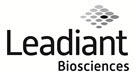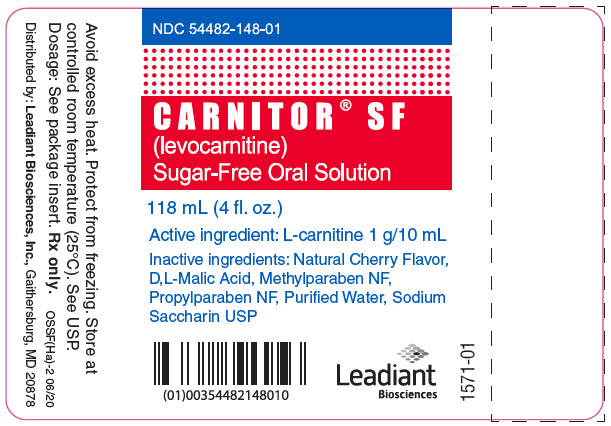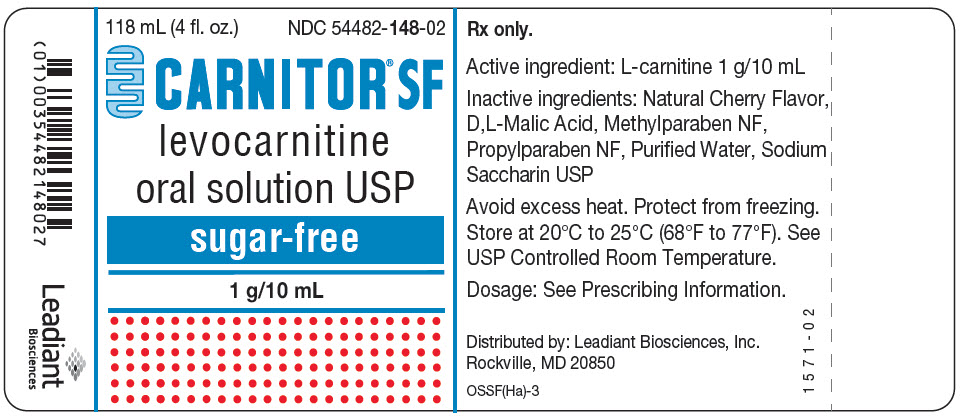 DRUG LABEL: Carnitor SF
NDC: 54482-148 | Form: SOLUTION
Manufacturer: Leadiant Biosciences, Inc.
Category: prescription | Type: HUMAN PRESCRIPTION DRUG LABEL
Date: 20241104

ACTIVE INGREDIENTS: LEVOCARNITINE 1 g/10 mL
INACTIVE INGREDIENTS: MALIC ACID; WATER; SACCHARIN SODIUM; METHYLPARABEN; PROPYLPARABEN

CARNITOR® SF (levocarnitine) Sugar-Free Oral Solution (1 g per 10 mL multidose)

For oral use only. Not for parenteral use.

DESCRIPTION

CARNITOR® (levocarnitine) is a carrier molecule in the transport of long-chain fatty acids across the inner mitochondrial membrane.

The chemical name of levocarnitine is 3-carboxy-2(R)-hydroxy-N,N,N-trimethyl-1-propanaminium, inner salt. Levocarnitine is a white crystalline, hygroscopic powder. It is readily soluble in water, hot alcohol, and insoluble in acetone. The specific rotation of levocarnitine is between -29° and -32°. Its chemical structure is:

Empirical Formula: C7H15NO3

Molecular Weight: 161.20

Each CARNITOR® (levocarnitine) Tablet contains 330 mg of levocarnitine and the inactive ingredients magnesium stearate, microcrystalline cellulose and povidone.

Each 118 mL container of CARNITOR® (levocarnitine) Oral Solution contains 1 g of levocarnitine/10 mL. Also contains: Artificial Cherry Flavor, D,L,-Malic Acid, Purified Water, Sucrose. Methylparaben NF and Propylparaben NF are added as preservatives. The pH is approximately 5.

Each 118 mL container of CARNITOR® SF (levocarnitine) Sugar-Free Oral Solution contains 1 g of levocarnitine/10 mL. Also contains: Natural Cherry Flavor, D,L,-Malic Acid, Purified Water, Sodium Saccharin USP. Methylparaben NF and Propylparaben NF are added as preservatives. The pH is approximately 5.

CLINICAL PHARMACOLOGY

CARNITOR® (levocarnitine) is a naturally occurring substance required in mammalian energy metabolism. It has been shown to facilitate long-chain fatty acid entry into cellular mitochondria, thereby delivering substrate for oxidation and subsequent energy production. Fatty acids are utilized as an energy substrate in all tissues except the brain. In skeletal and cardiac muscle, fatty acids are the main substrate for energy production.

Primary systemic carnitine deficiency is characterized by low concentrations of levocarnitine in plasma, RBC, and/or tissues. It has not been possible to determine which symptoms are due to carnitine deficiency and which are due to an underlying organic acidemia, as symptoms of both abnormalities may be expected to improve with CARNITOR®. The literature reports that carnitine can promote the excretion of excess organic or fatty acids in patients with defects in fatty acid metabolism and/or specific organic acidopathies that bioaccumulate acylCoA esters.^1-6

Secondary carnitine deficiency can be a consequence of inborn errors of metabolism. CARNITOR® may alleviate the metabolic abnormalities of patients with inborn errors that result in accumulation of toxic organic acids. Conditions for which this effect has been demonstrated are: glutaric aciduria II, methyl malonic aciduria, propionic acidemia, and medium chain fatty acylCoA dehydrogenase deficiency.^7,8 Autointoxication occurs in these patients due to the accumulation of acylCoA compounds that disrupt intermediary metabolism. The subsequent hydrolysis of the acylCoA compound to its free acid results in acidosis which can be life-threatening. Levocarnitine clears the acylCoA compound by formation of acylcarnitine, which is quickly excreted. Carnitine deficiency is defined biochemically as abnormally low plasma concentrations of free carnitine, less than 20 µmol/L at one week post term and may be associated with low tissue and/or urine concentrations. Further, this condition may be associated with a plasma concentration ratio of acylcarnitine/levocarnitine greater than 0.4 or abnormally elevated concentrations of acylcarnitine in the urine. In premature infants and newborns, secondary deficiency is defined as plasma levocarnitine concentrations below age-related normal concentrations.

PHARMACOKINETICS

In a relative bioavailability study in 15 healthy adult male volunteers, CARNITOR® Tablets were found to be bio-equivalent to CARNITOR® Oral Solution. Following 4 days of dosing with 6 tablets of CARNITOR® 330 mg b.i.d. or 2 g of CARNITOR® oral solution b.i.d., the maximum plasma concentration (Cmax) was about 80 µmol/L and the time to maximum plasma concentration (Tmax) occurred at 3.3 hours.

The plasma concentration profiles of levocarnitine after a slow 3 minute intravenous bolus dose of 20 mg/kg of CARNITOR® were described by a two-compartment model. Following a single i.v. administration, approximately 76% of the levocarnitine dose was excreted in the urine during the 0-24h interval. Using plasma concentrations uncorrected for endogenous levocarnitine, the mean distribution half life was 0.585 hours and the mean apparent terminal elimination half life was 17.4 hours.

The absolute bioavailability of levocarnitine from the two oral formulations of CARNITOR®, calculated after correction for circulating endogenous plasma concentrations of levocarnitine, was 15.1 ± 5.3% for CARNITOR® Tablets and 15.9 ± 4.9% for CARNITOR® Oral Solution.

Total body clearance of levocarnitine (Dose/AUC including endogenous baseline concentrations) was a mean of 4.00 L/h.

Levocarnitine was not bound to plasma protein or albumin when tested at any concentration or with any species including the human.^9

METABOLISM AND EXCRETION

In a pharmacokinetic study where five normal adult male volunteers received an oral dose of [^3H-methyl]-L-carnitine following 15 days of a high carnitine diet and additional carnitine supplement, 58 to 65% of the administered radioactive dose was recovered in the urine and feces in 5 to 11 days. Maximum concentration of [^3H-methyl]-L-carnitine in serum occurred from 2.0 to 4.5 hr after drug administration. Major metabolites found were trimethylamine N-oxide, primarily in urine (8% to 49% of the administered dose) and [^3H]-γ-butyrobetaine, primarily in feces (0.44% to 45% of the administered dose). Urinary excretion of levocarnitine was about 4 to 8% of the dose. Fecal excretion of total carnitine was less than 1% of the administered dose.^10

After attainment of steady state following 4 days of oral administration of CARNITOR® Tablets (1980 mg q12h) or Oral Solution (2000 mg q12h) to 15 healthy male volunteers, the mean urinary excretion of levocarnitine during a single dosing interval (12h) was about 9% of the orally administered dose (uncorrected for endogenous urinary excretion).

INDICATIONS AND USAGE

CARNITOR® (levocarnitine) is indicated in the treatment of primary systemic carnitine deficiency. In the reported cases, the clinical presentation consisted of recurrent episodes of Reye-like encephalopathy, hypoketotic hypoglycemia, and/or cardiomyopathy. Associated symptoms included hypotonia, muscle weakness and failure to thrive. A diagnosis of primary carnitine deficiency requires that serum, red cell and/or tissue carnitine levels be low and that the patient does not have a primary defect in fatty acid or organic acid oxidation (see CLINICAL PHARMACOLOGY). In some patients, particularly those presenting with cardiomyopathy, carnitine supplementation rapidly alleviated signs and symptoms. Treatment should include, in addition to carnitine, supportive and other therapy as indicated by the condition of the patient.

CARNITOR® (levocarnitine) is also indicated for acute and chronic treatment of patients with an inborn error of metabolism which results in a secondary carnitine deficiency.

CONTRAINDICATIONS

None known.

WARNINGS

Hypersensitivity Reactions

Serious hypersensitivity reactions, including rash, urticarial, and facial edema have been reported with oral CARNITOR®. Other serious hypersensitivity reactions, including anaphylaxis, laryngeal edema, and bronchospasm have been reported following intravenous levocarnitine administration, mostly in patients with end stage renal disease undergoing dialysis.

Discontinue use of CARNITOR® and instruct patients to seek medical attention if they experience symptoms suggestive of a hypersensitivity reaction.

PRECAUTIONS

General

CARNITOR® (levocarnitine) Oral Solution and CARNITOR® SF (levocarnitine) Sugar-Free Oral Solution are for oral/internal use only.

Not for parenteral use.

Gastrointestinal reactions may result from a too rapid consumption of carnitine. CARNITOR® (levocarnitine) Oral Solution and CARNITOR® SF (levocarnitine) Sugar-Free Oral Solution may be consumed alone, or dissolved in drinks or other liquid foods to reduce taste fatigue. They should be consumed slowly and doses should be spaced evenly throughout the day to maximize tolerance.

The safety and efficacy of oral levocarnitine has not been evaluated in patients with renal insufficiency. Chronic administration of high doses of oral levocarnitine in patients with severely compromised renal function or in ESRD patients on dialysis may result in accumulation of the potentially toxic metabolites, trimethylamine (TMA) and trimethylamine-N-oxide (TMAO), since these metabolites are normally excreted in the urine.

Drug Interactions

Reports of INR increase with the use of warfarin have been observed. It is recommended that INR levels be monitored in patients on warfarin therapy after the initiation of treatment with levocarnitine or after dose adjustments.

Carcinogenesis, Mutagenesis, Impairment of Fertility

Mutagenicity tests performed in Salmonella typhimurium, Saccharomyces cerevisiae, and Schizosaccharomyces pombe indicate that levocarnitine is not mutagenic. No long-term animal studies have been performed to evaluate the carcinogenic potential of levocarnitine.

Pregnancy

Reproductive studies have been performed in rats and rabbits at doses up to 3.8 times the human dose on the basis of surface area and have revealed no evidence of impaired fertility or harm to the fetus due to CARNITOR®. There are, however, no adequate and well controlled studies in pregnant women.

Because animal reproduction studies are not always predictive of human response, this drug should be used during pregnancy only if clearly needed.

Nursing Mothers

Levocarnitine supplementation in nursing mothers has not been specifically studied.

Studies in dairy cows indicate that the concentration of levocarnitine in milk is increased following exogenous administration of levocarnitine. In nursing mothers receiving levocarnitine, any risks to the child of excess carnitine intake need to be weighed against the benefits of levocarnitine supplementation to the mother. Consideration may be given to discontinuation of nursing or of levocarnitine treatment.

Pediatric Use

See DOSAGE AND ADMINISTRATION.

ADVERSE REACTIONS

The following adverse reactions associated with the use of oral formulations of levocarnitine were identified in clinical trials or postmarketing reports. Because these reactions were reported voluntarily from a population of uncertain size, it is not always possible to estimate their frequency, reliability, or to establish a causal relationship to drug exposure.

Gastrointestinal Reactions: Various mild gastrointestinal complaints have been reported during the long-term administration of oral L- or D,L-carnitine; these include transient nausea and vomiting, abdominal cramps, and diarrhea. Gastrointestinal adverse reactions with CARNITOR® (levocarnitine) Oral Solution or CARNITOR® SF (levocarnitine) Sugar-Free Oral Solution dissolved in liquids might be avoided by a slow consumption of the solution or by a greater dilution. Decreasing the dosage often diminishes or eliminates drug-related patient body odor or gastrointestinal symptoms when present. Tolerance should be monitored very closely during the first week of administration, and after any dosage increases.

Musculoskeletal Reactions: Mild myasthenia has been described only in uremic patients receiving D,L-carnitine.

Neurologic Reactions: Seizures have been reported to occur in patients with or without pre-existing seizure activity receiving either oral or intravenous levocarnitine. In patients with pre-existing seizure activity, an increase in seizure frequency and/or severity has been reported.

Hypersensitivity Reactions: Rash, urticaria, and facial edema have been reported with oral CARNITOR® (see WARNINGS).

OVERDOSAGE

There have been no reports of toxicity from levocarnitine overdosage. Levocarnitine is easily removed from plasma by dialysis. The intravenous LD50 of levocarnitine in rats is 5.4 g/kg and the oral LD50 of levocarnitine in mice is 19.2 g/kg. Large doses of levocarnitine may cause diarrhea.

DOSAGE AND ADMINISTRATION

CARNITOR® (levocarnitine) Tablets.

Adults: The recommended oral dosage for adults is 990 mg two or three times a day using the 330 mg tablets, depending on clinical response.

Infants and children: The recommended oral dosage for infants and children is between 50 and 100 mg/kg/day in divided doses, with a maximum of 3 g/day. Dosage should begin at 50 mg/kg/day. The exact dosage will depend on clinical response.

Monitoring should include periodic blood chemistries, vital signs, plasma carnitine concentrations and overall clinical condition.

CARNITOR® (levocarnitine) Oral Solution and CARNITOR® SF (levocarnitine) Sugar-Free Oral Solution.

For oral use only. Not for parenteral use.

Adults: The recommended dosage of levocarnitine is 1 to 3 g/day for a 50 kg subject, which is equivalent to 10 to 30 mL/day of CARNITOR® (levocarnitine) Oral Solution or CARNITOR® SF (levocarnitine) Sugar-Free Oral Solution. Higher doses should be administered only with caution and only where clinical and biochemical considerations make it seem likely that higher doses will be of benefit. Dosage should start at 1 g/day, (10 mL/day), and be increased slowly while assessing tolerance and therapeutic response. Monitoring should include periodic blood chemistries, vital signs, plasma carnitine concentrations, and overall clinical condition.

Infants and children: The recommended dosage of levocarnitine is 50 to 100 mg/kg/day which is equivalent to 0.5 mL/kg/day CARNITOR® (levocarnitine) Oral Solution or CARNITOR® SF (levocarnitine) Sugar-Free Oral Solution. Higher doses should be administered only with caution and only where clinical and biochemical considerations make it seem likely that higher doses will be of benefit. Dosage should start at 50 mg/kg/day, and be increased slowly to a maximum of 3 g/day (30 mL/day) while assessing tolerance and therapeutic response. Monitoring should include periodic blood chemistries, vital signs, plasma carnitine concentrations, and overall clinical condition.

CARNITOR® (levocarnitine) Oral Solution or CARNITOR® SF (levocarnitine) Sugar-Free Oral Solution may be consumed alone or dissolved in drink or other liquid food. Doses should be spaced evenly throughout the day (every three or four hours) preferably during or following meals and should be consumed slowly in order to maximize tolerance.

HOW SUPPLIED

STORAGE AND HANDLING

CARNITOR® (levocarnitine) Tablets are supplied as 330 mg tablets embossed with "CARNITOR ST" in individual blisters, packaged in boxes of 90 (NDC 54482-144-07). Store in original packaging: content hygroscopic. Store at 20°C to 25°C (68°F to 77°F). See USP Controlled Room Temperature. CARNITOR® (levocarnitine) Tablets are distributed by Leadiant Biosciences, Inc.

CARNITOR® (levocarnitine) Oral Solution is supplied in 118 mL (4 FL. OZ.) plastic containers (NDC 54482-145-08 and NDC 54482-145-09). Store at 20°C to 25°C (68°F to 77°F). See USP Controlled Room Temperature. Avoid excessive heat and protect from freezing. CARNITOR® (levocarnitine) Oral Solution is distributed by Leadiant Biosciences, Inc.

CARNITOR® SF (levocarnitine) Sugar-Free Oral Solution is supplied in 118 mL (4 FL. OZ.) plastic containers (NDC 54482-148-01 and NDC 54482-148-02). Store at 20°C to 25°C (68°F to 77°F). See USP Controlled Room Temperature. Avoid excessive heat and protect from freezing. CARNITOR® SF (levocarnitine) Sugar-Free Oral Solution is distributed by Leadiant Biosciences, Inc.

Rx only.

REFERENCES

1. Bohmer, T., Rydning, A. and Solberg, H.E. 1974. Carnitine levels in human serum in health and disease. Clin. Chim. Acta 57:55-61.
2. Brooks, H., Goldberg, L., Holland, R. et al. 1977. Carnitine-induced effects on cardiac and peripheral hemodynamics. J. Clin. Pharmacol. 17:561-568.
3. Christiansen, R., Bremer, J. 1976. Active transport of butyrobetaine and carnitine into isolated liver cells. Biochim. Biophys. Acta 448:562-577.
4. Lindstedt, S. and Lindstedt, G. 1961. Distribution and excretion of carnitine in the rat. Acta Chem. Scand. 15:701-702.
5. Rebouche, C.J. and Engel, A.G. 1983. Carnitine metabolism and deficiency syndromes. Mayo Clin. Proc. 58:533-540.
6. Rebouche, C.J. and Paulson, D.J. 1986. Carnitine metabolism and function in humans. Ann. Rev. Nutr. 6:41-66.
7. Scriver, C.R., Beaudet, A.L., Sly, W.S. and Valle, D. 1989. The Metabolic Basis of Inherited Disease. New York: McGraw-Hill.
8. Schaub, J., Van Hoof, F. and Vis, H.L. 1991. Inborn Errors of Metabolism. New York: Raven Press.
9. Marzo, A., Arrigoni Martelli, E., Mancinelli, A., Cardace, G., Corbelletta, C., Bassani, E. and Solbiati, M. 1991. Protein binding of L-carnitine family components. Eur. J. Drug Met. Pharmacokin. Special Issue III: 364-368.
10. Rebouche, C.J. 1991. Quantitative estimation of absorption and degradation of a carnitine supplement by human adults. Metabolism 40:1305-1310.

PREVIOUS EDITION IS OBSOLETE
Date of Issue: 07/23
OPI-16

PRINCIPAL DISPLAY PANEL - 118 mL Bottle Label

NDC 54482-148-01

CARNITOR® SF
(levocarnitine)
Sugar-Free Oral Solution

118 mL (4 fl. oz.)

Active ingredient: L-carnitine 1 g/10 mL

Inactive ingredients: Natural Cherry Flavor,
D,L-Malic Acid, Methylparaben NF,
Propylparaben NF, Purified Water, Sodium
Saccharin USP

Leadiant
Biosciences

Avoid excess heat. Protect from freezing. Store at
controlled room temperature (25°C). See USP.
Dosage: See package insert. Rx only.

OSSF(Ha)-2 06/20

Distributed by: Leadiant Biosciences, Inc., Gaithersburg, MD 20878

1571-01

PRINCIPAL DISPLAY PANEL - 118 mL Bottle Label - NDC 54482-148-02

118 mL (4 fl. oz.)
NDC 54482-148-02

CARNITOR® SF
levocarnitine
oral solution USP
sugar-free

1 g/10 mL

Rx only.

Active ingredient: L-carnitine 1 g/10 mL

Inactive ingredients: Natural Cherry Flavor,
D,L-Malic Acid, Methylparaben NF,
Propylparaben NF, Purified Water, Sodium
Saccharin USP

Avoid excess heat. Protect from freezing.
Store at 20°C to 25°C (68°F to 77°F). See
USP Controlled Room Temperature.

Dosage: See Prescribing Information.

Distributed by: Leadiant Biosciences, Inc.
Rockville, MD 20850

OSSF(Ha)-3

1571-02